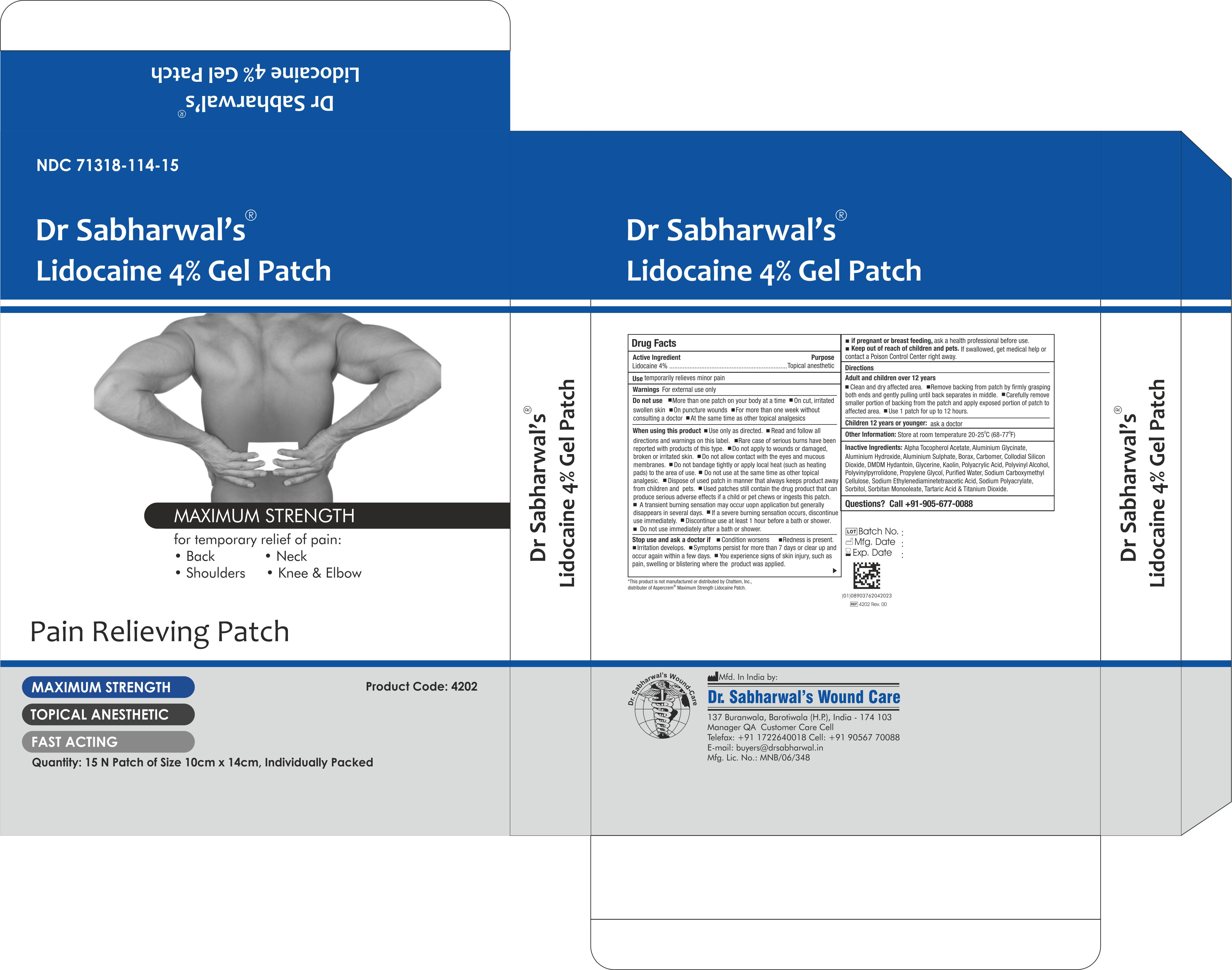 DRUG LABEL: Dr Sabharwals
NDC: 71318-114 | Form: PATCH
Manufacturer: Dr. Sabharwal's Wound Care
Category: otc | Type: HUMAN OTC DRUG LABEL
Date: 20260124

ACTIVE INGREDIENTS: LIDOCAINE 224 mg/1 1
INACTIVE INGREDIENTS: ALUMINIUM SULFATE OCTADECAHYDRATE; BORAX; PROPYLENE GLYCOL; DIHYDROXYALUMINUM AMINOACETATE; SORBITAN MONOOLEATE; DMDM HYDANTOIN; SODIUM POLYACRYLATE (8000 MW); POLYVINYL ALCOHOL (100000 MW); POLYACRYLIC ACID (250000 MW); TITANIUM DIOXIDE; ALUMINUM HYDROXIDE; ALPHA-TOCOPHEROL ACETATE; TARTARIC ACID; WATER; GLYCERIN; KAOLIN; BUTYLATED HYDROXYTOLUENE; POVIDONE; EDETATE DISODIUM; CARBOXYMETHYLCELLULOSE SODIUM

ACTIVE INGREDIENT

Lidocaine 4%

INDICATIONS AND USAGE

Temporarily Relieves Minor Pain

PURPOSE

Topical Anesthetic

WARNINGS

For external use only

DO NOT USE

- More than one patch on your body at a time
- On cut, irritated swollen skin
- On puncture wounds
- For more than one week without consulting a doctor
- At the same time as other topical analgesics

WHEN USING

- Use only as directed.
- Read and follow all directions and warnings on this label.
- Rare case of serious burns have been reported with products of this type.
- Do not apply to wounds or damaged, broken or irritated skin.
- Do not allow contact with the eyes and mucous membranes.
- Do not bandage tightly or apply local heat (such as heating pads) to the area of use.
- Do not use at the same time as other topical analgesic.
- Dispose of used patch in manner that always keeps product away from children and pets.
- Used patches still contain the drug product that can produce serious adverse effects if a child or pet chews or ingests this patch
- A transient burning sensation may occur uopn application but generally disappears in several days.
- If a severe burning sensation occurs, discontinue use immediately.
- Discontinue use at least 1 hour before a bath or shower.
- Do not use immediately after a bath or shower.

ASK DOCTOR

Condition worsens
Redness is present.
Irritation develops.
Symptoms persist for more than 7 days or clear up and occur again within a few days.
You experience signs of skin injury, such as pain, swelling or blistering where the product was applied.

PREGNANCY OR BREAST FEEDING

ask a health professional before use.

KEEP OUT OF REACH OF CHILDREN

If swallowed, get medical help or contact a Poison Control Center right away.

INSTRUCTIONS FOR USE

Adult and children over 12 years
Clean and dry affected area.
Remove backing from patch by firmly grasping both ends and gently pulling until back separates in middle.
Carefully remove smaller portion of backing from the patch and apply exposed portion of patch to affected area.
Use 1 patch for up to 12 hours.

Children 12 years or younger:
ask a doctor

STORAGE AND HANDLING

Store at room temperature 20-25^0C (68-77^0F)

INACTIVE INGREDIENT

Alpha Tocopherol Acetate, Aluminium Glycinate, Aluminium Hydroxide, Aluminium Sulphate, Borax, Carbomer, Collodial Silicon
Dioxide, DMDM Hydantoin, Glycerine, Kaolin, Polyacrylic Acid, Polyvinyl Alcohol, Polyvinylpyrrolidone, Propylene Glycol, Purified Water, Sodium Carboxymethyl Cellulose, Sodium Ethylenediaminetetraacetic Acid, Sodium Polyacrylate, Sorbitol, Sorbitan Monooleate, Tartaric Acid & Titanium Dioxide.

Questions? Call +91-718-739-5680

DOSAGE AND ADMINISTRATION

Topical Patch for External Use Only